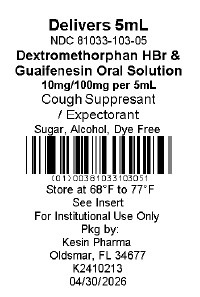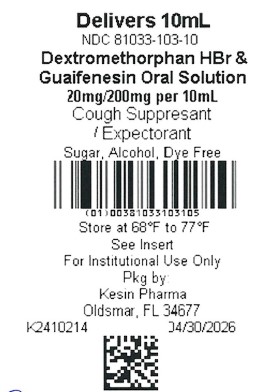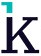 DRUG LABEL: Dextromethorphan HBr and Guaifenesin Oral Solution
NDC: 81033-103 | Form: LIQUID
Manufacturer: KESIN PHARMA CORPORATION
Category: otc | Type: HUMAN OTC DRUG LABEL
Date: 20250130

ACTIVE INGREDIENTS: GUAIFENESIN 100 mg/5 mL; DEXTROMETHORPHAN HYDROBROMIDE 10 mg/5 mL
INACTIVE INGREDIENTS: PROPYLENE GLYCOL; ANHYDROUS CITRIC ACID; PROPYLPARABEN; WATER; SUCRALOSE; METHYLPARABEN; SORBITOL; POTASSIUM CITRATE; AMMONIUM GLYCYRRHIZATE

Dextromethorphan HBr and Guaifenesin Oral Solution

Dextromethorphan HBr and Guaifenesin Oral Solution 5 and 10 mL

Disclaimer: Most OTC drugs are not reviewed and approved by the FDA, however, they may be marketed if they comply with applicable regulations and policies. FDA has not evaluated whether this product complies.

DM Guaifenesin
Non-Narcotic, Sugar, Dye and Alcohol Free
Cough Suppressant/Expectorant

DESCRIPTION

Each 5 mL (1 teaspoonful) contains:

Dextromethorphan Hydrobromide 10 mg

Guaifenesin 100 mg

Each 10 mL (2 teaspoonfuls) contains:

Dextromethorphan Hydrobromide 20 mg

Guaifenesin 200 mg

Inactive Ingredients

Inactive Ingredients: citric acid, grape flavor, methylparaben, monoammonium glycrrhizate, potassium citrate, propylene glycol, propylparaban,purified water, sorbitol, sucralose.

USES

- temporarily relieves cough due to minor throat and bronchial irritation as may occur with a cold

- helps loosen phlegm (mucus) and thin bronchial secretions to make coughs more productive

WARNINGS

Do not use if you are now taking a prescription monoamine oxidase inhibitor (MAOI) (certain drugs for depression, psychiatric, or emotional conditions, or Parkinson’s disease), or for 2 weeks after stopping the MAOI drug. If you do not know if your prescription drug contains an MAOI, ask a doctor or pharmacist before taking this product.

Ask a doctor before use if you have

- Cough that occurs with too much phlegm (mucus)
- Cough that lasts or is chronic such as occurs with smoking, asthma, chronic bronchitis, or emphysema.

Stop use and ask a doctor if

- cough lasts more than 7 days, comes back, or is accompanied by fever, rash, or persistent headache. These could be signs of a serious condition.
- you are hypersensitive to any of the ingredients.

If pregnant or breast-feeding, ask a health professional before use.

Keep out of reach of children. In case of overdose, get medical help or contact a Poison Control Center right away.

Professional Note: Guaifenesin has been shown to produce a color interference with certain clinical laboratory determinations of 5-hydroxyindoleacetic acid (5-HIAA) and vanillylmandelic acid (VMA)

DIRECTIONS

Follow dosage table below or use as directed by a
physician

- Do not take more than 6 doses in any 24-hour period

Age | Dose
adults and children 12 years and over | 10mL (2 teaspoonful) every 4 hours
children 6 to under 12 years of age | 5mL (1 teaspoonful) every 4 hours
children 2 to under 6 years of age | 2.5mL (1/2 teaspoonful) every 4 hours
children under 2 years | consult a doctor

HOW SUPPLIED

Dextromethorphan hydrobromide and Guaifenesin is a clear, grape flavor solution supplied in the following oral dosage forms:
5 mL unit dose cup:
NDC 81033-103-05
Case containing 100 units dose cups of 5 mL:
NDC 81033-103-50

10 mL unit dose cups:
NDC 81033-103-10
Case containing 100 unit dose cups of 10 mL:
NDC 81033-103-51

STORAGE

Store at controlled temperature 15°C to 30°C (59°F to 86°F) [See USP]. Protect from light.

QUESTIONS OR COMMENTS

Call 1-833-537-4679

Packaged by:
Kesin Pharma
Oldsmar, FL 34677
Effective 10/2024
Revision 03

PRINCIPAL DISPLAY PANEL - 5 mL Unit Dose Cup Label

NDC 81033-103-05

Dextromethorphan HBr and Guaifenesin Oral Solution

Delivers 10mg/100mg per 5mL

FOR INSTITUTIONAL USE ONLY

Store at 59°F to 86°F (15°C to 30°C)

PRINCIPAL DISPLAY PANEL - 10 mL Unit Dose Cup Label

NDC 81033-103-10

Dextromethorphan HBr and Guaifenesin Oral Solution

Delivers 20mg/200mg per 10mL

FOR INSTITUTIONAL USE ONLY

Store at 59°F to 86°F (15°C to 30°C)